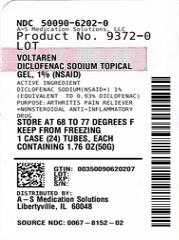 DRUG LABEL: VOLTAREN ARTHRITIS PAIN
NDC: 50090-6202 | Form: GEL
Manufacturer: A-S Medication Solutions
Category: otc | Type: HUMAN OTC DRUG LABEL
Date: 20240530

ACTIVE INGREDIENTS: DICLOFENAC SODIUM 10 mg/1 g
INACTIVE INGREDIENTS: AMMONIA; CARBOMER HOMOPOLYMER TYPE C (ALLYL PENTAERYTHRITOL CROSSLINKED); COCO-CAPRYLATE/CAPRATE; ISOPROPYL ALCOHOL; MINERAL OIL; POLYOXYL 20 CETOSTEARYL ETHER; PROPYLENE GLYCOL; WATER

VOLTAREN ARTHRITIS PAIN

Active ingredient

Diclofenac sodium (NSAID*) 1% (equivalent to 0.93% diclofenac)

*nonsteroidal anti-inflammatory drug

Purpose

Arthritis pain reliever

Uses

- for the temporary relief of arthritis pain ONLY inthe following areas:
  - hand, wrist, elbow (upper body areas)
  - foot, ankle, knee (lower body areas)
- this product may take up to 7 days to work for arthritis pain; it is not for immediate relief. If no pain relief in 7 days, stop use.

Warnings

For external use only

Allergy alert:Diclofenac may cause a severe allergic reaction, especially in people allergic to aspirin.

Symptoms may include:

- hives
- asthma (wheezing)
- skin reddening
- blisters
- facial swelling
- shock
- rash

If an allergic reaction occurs, stop use and seek medical help right away.

Liver warning:This product contains diclofenac. Liver damage may occur if you apply

- more or for a longer time than directed
- when using other drugs containing diclofenac

Stomach bleeding warning:This product contains an NSAID, which may cause severe stomach bleeding. The chance is small but higher if you

- are age 60 or older
- have had stomach ulcers or bleeding problems
- take a blood thinning (anticoagulant) or steroid drug
- take other drugs containing prescription or nonprescription NSAIDs (aspirin, ibuprofen, naproxen, or others)
- have 3 or more alcoholic drinks every day while using this product
- apply more or for longer than directed

Heart attack and stroke warning:NSAIDs, except aspirin, increase the risk of heart attack, heart failure, and stroke. These can be fatal. The risk is higher if you use more than directed or for longer than directed.

Do not use

- if you have ever had an allergic reaction to any other pain reliever or to a fever reducer
- for strains, sprains, bruises or sports injuries. This product has not been shown to work for these types of injuries.
- right before or after heart surgery
- on more than 2 body areas at the same time
- in the eyes, nose or mouth

Ask a doctor before use if

- you have problems or serious side effects from taking pain relievers or fever reducers
- stomach bleeding warning applies to you
- you have a history of stomach problems, such as heartburn
- you have high blood pressure, heart disease, liver cirrhosis, kidney disease, asthma, or had a stroke
- you are taking a diuretic
- you are under age 18 years. It is not known if this drug works or is safe in children under age 18 years.

Ask a doctor or pharmacist before use if you are

- under a doctor’s care for any serious condition
- taking any other drug

When using this product

- avoid contact with eyes, nose, or mouth
- if eye contact occurs, rinse thoroughly with water

Stop use and ask a doctor if

- pain gets worse or lasts more than 21 days
- redness or swelling is present in the painful area
- fever occurs
- skin irritation occurs
- any new symptoms appear. These could be signs of a serious condition.
- you experience any of the following signs of stomach bleeding:
  - feel faint
  - have bloody or black stools
  - vomit blood
  - have stomach pain that does not get better
- you have symptoms of heart problems or stroke:
  - chest pain
  - trouble breathing
  - leg swelling
  - weakness in one part or side of body
  - slurred speech

If pregnant or breast-feeding,

ask a health professional before use. It is especially important not to use diclofenac at 20 weeks or later in pregnancy unless definitely directed to do so by a doctor because it may cause problems in the unborn child or complications during delivery.

Directions

Use up to 21 days unless directed by your doctor

Not for strains, sprains, bruises, or sports injuries. This product has not been shown to work for these types of injuries.

Daily | Per Dose
For your arthritis pain:; - • Use 4 times per day every day - • Do not use on more than 2 body areas at the same time | Use ENCLOSED DOSING CARD to measure a dose; - • For each upper body area (hand, wrist, or elbow) – Squeeze out 2.25 inches (2 grams) - • For each lower body area (foot, ankle or knee) – Squeeze out 4.5 inches (4 grams)

Read the enclosed User Guidefor complete instructions:

- use only as directed
- do not use more than directed or for longer than directed
- apply only to clean, dry skin that does not have any cuts, open wounds, infections or rashes
- do not apply in same area as any other product
- do not apply with external heat such as heating pad
- do not apply a bandage over the treated area
- store ENCLOSED DOSING CARD with your Voltaren Arthritis Pain. The dosing card is
  re-usable.

Other information

- store at 20-25°C (68-77°F). Keep from freezing.
- read all product information before using. Keep the dosing card, this carton and accompanying User Guide for important information.

Inactive ingredients

carbomer homopolymer Type C, cocoyl caprylocaprate, fragrance, isopropyl alcohol, mineral oil, polyoxyl 20 cetostearyl ether, propylene glycol, purified water, strong ammonia solution

Questions or comments?

1-855-297-3031 www.voltarengel.com

Additional Information

ORIGINAL PRESCRIPTION STRENGTH

Medicated Gel Clinically Proven to Relieve Arthritis Pain

TREATMENT AREAS

- Hand Wrist Elbow Foot Ankle Knee
- Not for use on any other body area (such as back, hip, or shoulder)

TREATMENT AREAS

Use Enclosed Dosing Card to Measure a Dose

Voltaren ARTHRITIS PAIN

diclofenac sodium topical gel, 1% (NSAID) – arthritis pain reliever

Dosing Card (NOT ACTUAL SIZE)

Read product User Guide before use

Not for immediate pain relief

Upper body dose2.25 inches long (2 grams)

Lower body dose4.5 inches long (4 grams)

How to Use

- For arthritis pain only
- Use 4 times a day
- May take up to 7 days to work for your arthritis pain
- For use on no more than 2 body areas
- Use up to 21 days unless directed by your doctor
- Tamper evident statement: Do not use if safety seal on tube nozzle is broken or missing.

Medication Guide

Medication Guide for Nonsteroidal Anti-Inflammatory Drugs (NSAIDs)

What is the most important information I should know about medicines called Nonsteroidal Anti-Inflammatory Drugs (NSAIDs)?

NSAIDs can cause serious side effects, including:

- Increased risk of a heart attack or stroke that can lead to death. This risk may happen early in treatment and may increase:
  - with increasing doses of NSAIDs
  - with longer use of NSAIDs

Do not take NSAIDs right before or after a heart surgery called a “coronary artery bypass graft (CABG).”

Avoid taking NSAIDs after a recent heart attack, unless your healthcare provider tells you to. You may have an increased risk of another heart attack if you take NSAIDs after a recent heart attack.

- Increased risk of bleeding, ulcers, and tears (perforation) of the esophagus (tube leading from the mouth to the stomach), stomach and intestines:
  - anytime during use
  - without warning symptoms
  - that may cause death

The risk of getting an ulcer or bleeding increases with:

  - past history of stomach ulcers, or stomach or intestinal bleeding with use of NSAIDs
  - taking medicines called “corticosteroids”, “anticoagulants”, “SSRIs”, or “SNRIs
  - increasing doses of NSAIDs
  - older age
  - longer use of NSAID
  - poor health
  - smoking
  - advanced liver problems
  - drinking alcohol
  - bleeding problems

NSAIDs should only be used:

  - exactly as prescribed
  - at the lowest dose possible for your treatment
  - for the shortest time needed

What are NSAIDs?

NSAIDs are used to treat pain and redness, swelling, and heat (inflammation) from medical conditions such as different types of arthritis, menstrual cramps, and other types of short-term pain

Who should not take NSAIDs?

Do not take NSAIDs :

- if you had an asthma attack, hives, or other allergic reaction with aspirin or any other NSAIDs
- right before or after heart bypass surgery

Before taking NSAIDs, tell your healthcare provider about all of your medical conditions, including if you:

- have liver or kidney problems
- have high blood pressure
- have asthma
- are pregnant or plan to become pregnant. Talk to your healthcare provider if you are considering taking NSAIDs during pregnancy. You should not take NSAIDs after 29 weeks of pregnancy.
- Are breastfeeding or plan to breast feed

Tell your healthcare provider all of the medicines you take, including prescription or over-the-counter medicines, vitamins or herbal supplements. NSAIDs and some other medicines can interact with each other and cause serious side effects. Do not start taking any new medicine without talking to your healthcare provider first.

What are the possible side effects of NSAIDs?

NSAIDs can cause serious side effects, including:

See “What is the most important information I should know about medicines called Nonsteroidal Anti-inflammatory Drugs (NSAIDs)?”

- new or worse high blood pressure
- heart failure
- liver problems including liver failure
- kidney problems including kidney failure
- low red blood cells (anemia)
- life-threatening skin reactions
- life-threatening allergic reactions
- Other side effects of NSAIDs include: stomach pain, constipation, diarrhea, gas, heartburn, nausea, vomiting, and dizziness.

Get emergency help right away if you have any of the following symptoms:

- shortness of breath or trouble breathing
- slurred speech
- chest pain
- swelling of the face or throat
- weakness in one part or side of your body

Stop taking your NSAID and call your healthcare provider right away if you get any of the following symptoms:

- nausea
- vomit blood
- more tired or weaker than usual
- there is blood in your bowel movement or it is black and sticky like tar
- diarrhea
- itching
- unusual weight gain
- your skin or eyes look yellow
- skin rash or blisters with fever
- indigestion or stomach pain
- swelling of the arms, legs, hands and feet
- flu-like symptoms

If you take too much of your NSAID, call your healthcare provider or get medical help right away.

These are not all the possible side effects of NSAIDs. For more information, ask your healthcare provider or pharmacist about NSAIDs.

Call your doctor for medical advice about side effects. You may report side effects to FDA at 1-800-FDA-1088.

Other information about NSAIDs

- Aspirin is an NSAID but it does not increase the chance of a heart attack. Aspirin can cause bleeding in the brain, stomach, and intestines. Aspirin can also cause ulcers in the stomach and intestines.
- Some NSAIDs are sold in lower doses without a prescription (over-the-counter). Talk to your healthcare provider before using over-the-counter NSAIDs for more than 10 days.

General Information about the safe and effective use of NSAIDs

Medicines are sometimes prescribed for purposes other than those listed in a Medication Guide. Do not use NSAIDs for a condition for which it was not prescribed. Do not give NSAIDs to other people, even if they have the same symptoms that you have. It may harm them.

If you would like more information about NSAIDs, talk with your healthcare provider. You can ask your pharmacist or healthcare provider for information about NSAIDs that is written for health professionals.

This Medication Guide has been approved by the U.S. Food and Drug Administration.

Marketed by:

Endo Pharmaceuticals Inc., Malvern, PA 19355

Manufactured by:

Novartis Pharma Produktions GmbH,

Wehr, Germany for

Sandoz Inc., Princeton, NJ 08540

Revised: April 2016

HOW SUPPLIED

Product: 50090-6202

NDC: 50090-6202-0 50 g in a TUBE / 24 in a CASE